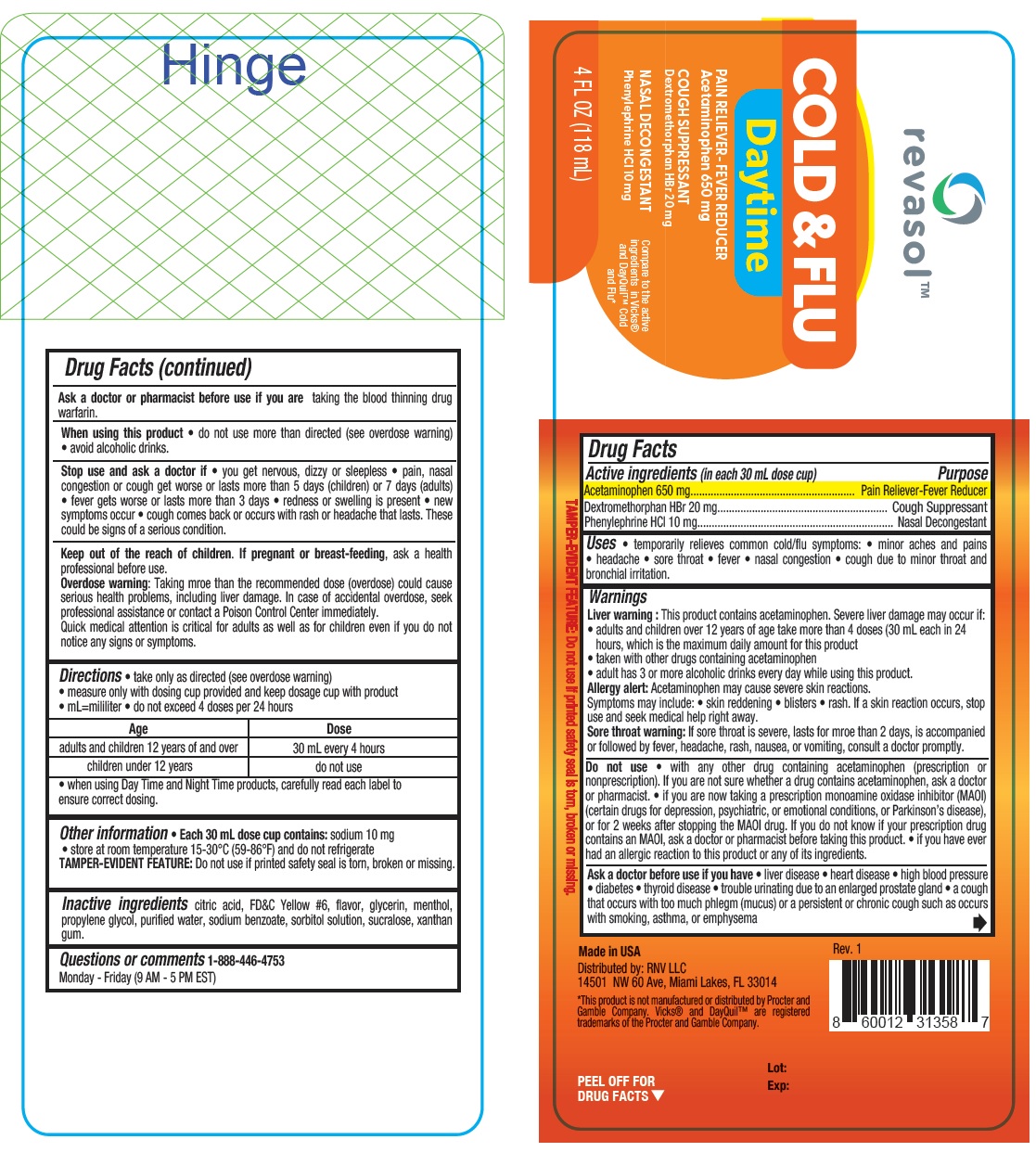 DRUG LABEL: REVASOL DAYTIME COLD AND FLU
NDC: 84379-275 | Form: LIQUID
Manufacturer: Rnv LLC
Category: otc | Type: HUMAN OTC DRUG LABEL
Date: 20250305

ACTIVE INGREDIENTS: PHENYLEPHRINE HYDROCHLORIDE 10 mg/30 mL; DEXTROMETHORPHAN HYDROBROMIDE 20 mg/30 mL; ACETAMINOPHEN 650 mg/30 mL
INACTIVE INGREDIENTS: WATER; XANTHAN GUM; GLYCERIN; SODIUM BENZOATE; PROPYLENE GLYCOL; CITRIC ACID; SORBITOL SOLUTION; SUCRALOSE; MENTHOL; FD&C YELLOW NO. 6

Revasol Daytime Cold & Flu

ACTIVE INGREDIENT

Active ingredients (in each 30 mL dose cup) Purpose

Acetaminophen 650mg....................................................Pain reliever-Fever reducer

Dextromethorphan HBr 20 mg.........................................Cough suppressant

Phenylephrine HCl 10 mg................................................Nasal decongestant

PURPOSE

Pain reliever/fever reducer

Cough suppressant

Nasal decongestant

Uses

• temporarily relieves common cold/flu symptoms: • minor aches and pains
• headache • sore throat • fever • nasal congestion • cough due to minor throat and
bronchial irritation.

Warnings

Liver warning: This product contains acetaminophen. Severe liver damage may occur if:
• adults and children over 12 years of age take more than 4 doses (30 mL each in 24
hours, which is the maximum daily amount for this product
• taken with other drugs containing acetaminophen
• adult has 3 or more alcoholic drinks every day while using this product.
Allergy alert: Acetaminophen may cause severe skin reactions.
Symptoms may include: • skin reddening • blisters • rash. If a skin reaction occurs, stop
use and seek medical help right away.
Sore throat warning: If sore throat is severe, lasts for more than 2 days, is accompanied
or followed by fever, headache, rash, nausea, or vomiting, consult a doctor promptly.

Do not use

• With any other drug containing acetaminophen (prescription or
nonprescription). If you are not sure whether a drug contains acetaminophen, ask a doctor
or pharmacist. • if you are now taking a prescription monoamine oxidase inhibitor (MAOI)
(certain drugs for depression, psychiatric, or emotional conditions, or Parkinson’s disease),
or for 2 weeks after stopping the MAOI drug. If you do not know if your prescription drug
contains an MAOI, ask a doctor or pharmacist before taking this product. • if you have ever
had an allergic reaction to this product or any of its ingredients.

Ask a doctor before use if you have

• liver disease • heart disease • high blood pressure
• diabetes • thyroid disease • trouble urinating due to an enlarged prostate gland • a cough
that occurs with too much phlegm (mucus) or a persistent or chronic cough such as occurs
with smoking, asthma, or emphysema

Ask a doctor or pharmacist before use if you are taking the blood thinning drug warfarin.

When using this product

• do not use more than directed (see overdose warning)
• avoid alcoholic drinks.

Stop use and ask a doctor if

• you get nervous, dizzy or sleepless • pain, nasal
congestion or cough get worse or lasts more than 5 days (children) or 7 days (adults)
• fever gets worse or lasts more than 3 days • redness or swelling is present • new
symptoms occur • cough comes back or occurs with rash or headache that lasts. These
could be signs of a serious condition.

KEEP OUT OF REACH OF CHILDREN

Keep out of the reach of children. If pregnant or breast-feeding, ask a health professional before use.

OVERDOSAGE

Overdose warning:

Taking more than the recommended dose (overdose) could cause
serious health problems, including liver damage. In case of accidental overdose, seek
professional assistance or contact a Poison Control Center immediately.
Quick medical attention is critical for adults as well as for children even if you do not
notice any signs or symptoms.

Directions

• take only as directed (see overdose warning)
• measure only with dosing cup provided and keep dosage cup with product
• mL=mililiter

• do not exceed 4 doses per 24 hours

Age | Dose
adults and children 12 years of and over | 30 mL every 4 hours
children under 12 years | do not use

- when using Day Time and Night Time products, carefully read each label to ensure correct dosing.

Other information

• Each 30 mL dose cup contains: sodium 10 mg
• store at room temperature 15-30°C (59-86°F) and do not refrigerate
TAMPER-EVIDENT FEATURE: Do not use if printed safety seal is torn, broken or missing.

Inactive ingredients

citric acid, FD&C Yellow #6, flavor, glycerin, menthol, propylene glycol, purified water, sodium benzoate, sorbitol solution, sucralose, xanthan gum.

Questions or comments 1-888-446-4753
Monday - Friday (9 AM - 5 PM EST)